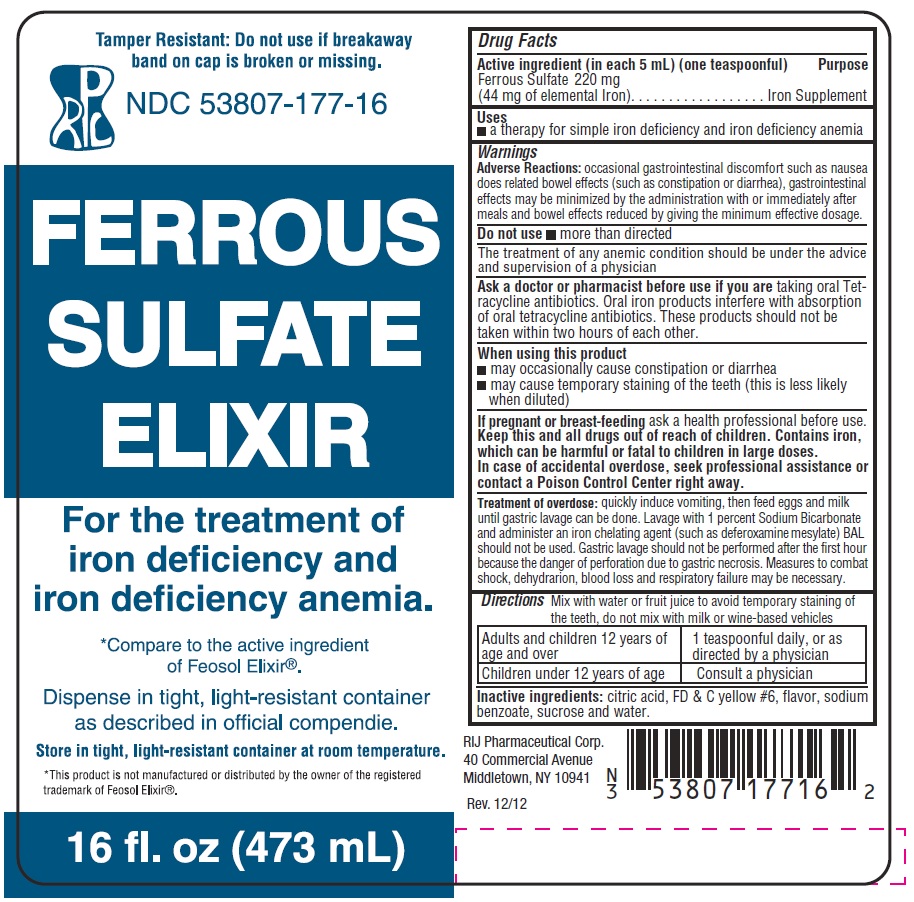 DRUG LABEL: FERROUS SULFATE
NDC: 53807-177 | Form: ELIXIR
Manufacturer: Rij Pharmaceutical Corporation
Category: otc | Type: HUMAN OTC DRUG LABEL
Date: 20180430

ACTIVE INGREDIENTS: FERROUS SULFATE 220 mg/5 mL
INACTIVE INGREDIENTS: CITRIC ACID MONOHYDRATE; FD&C YELLOW NO. 6; SODIUM BENZOATE; SUCROSE; WATER

Drug Facts

Active ingredient (in each 5 mL) (one teaspoonful)

Ferrous Sulfate 220 mg (44 mg of elemental Iron)

Purpose

Iron Supplement

Uses

a therapy for simple iron deficiency and iron deficiency anemia

Warnings

Adverse Reactions:

occasional gastrointestinal discomfort such as nausea dose related bowel effects (such as constipation or diarrhea), gastrointestinal effects may be minimized by the administration with or immediately after meals and bowel effects reduced by giving the minimum effective dosage.

Do not use

- more than directed

The treatment of any anemic condition should be under the advice and supervision of a physician

Ask a doctor or pharmacist before use if you are

taking oral Tetracycline antibiotics. Oral iron products interfere with absorption of oral tetracycline antibiotics. These products should not be taken within two hours of each other.

When using this product

- may occasionally cause constipation or diarrhea
- may cause temporary staining of the teeth (this is less likely when diluted)

If pregnant or breast-feeding

ask a health professional before use.

Keep this and all drugs out of reach of children.

Contains iron, which can be harmful or fatal to children in large doses. In case of accidental overdose, seek professional assistance or contact a Poison Control Center right away.

Treatment of overdose:

quickly induce vomiting, then feed eggs and milk until gastric lavage can be done. Lavage with 1 percent Sodium Bicarbonate and administer an iron chelating agent (such as deferoxamine mesylate) BAL should not be used. Gastric lavage should not be performed after the first hour because the danger of perforation due to gastric necrosis. Measures to combat shock, dehydration, blood loss and respiratory failure may be necessary.

Directions

Mix with water or fruit juice to avoid temporary staining of the teeth, do not mix with milk or wine-based vehicles

Adults and children 12 years of age and over | 1 teaspoonful daily, or as directed by a physician
Children under 12 years of age | Consult a physician

Inactive ingredients

citric acid, FD & C yellow #6, flavor, sodium benzoate, sucrose and water.

Other information

- Store in tight, light-resistant container at room temperature